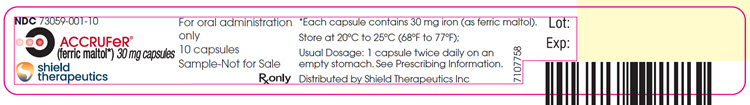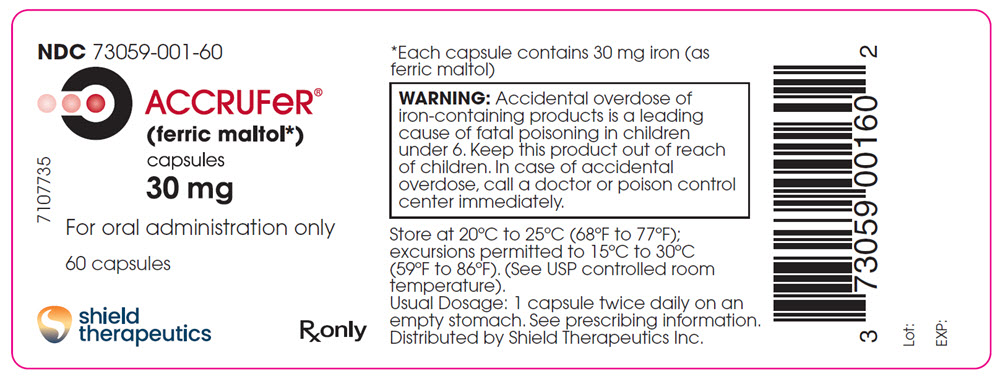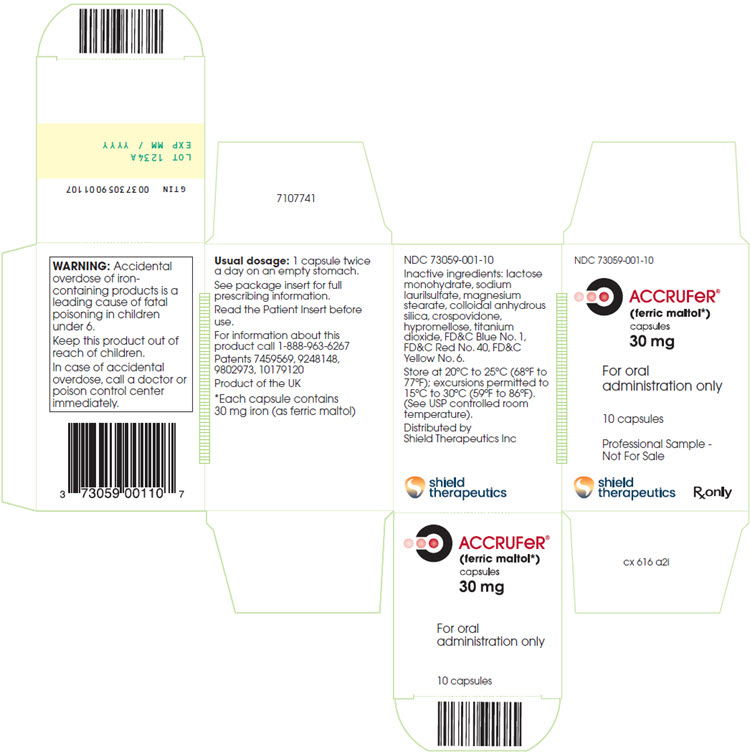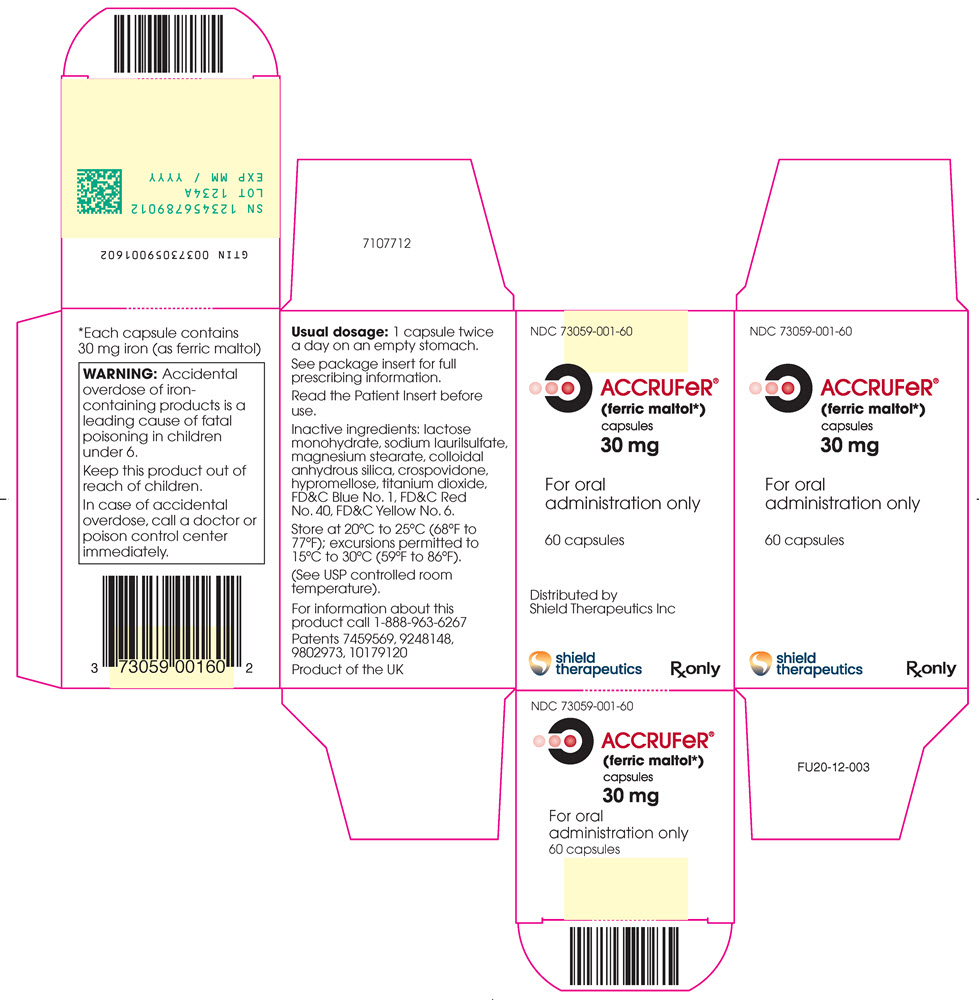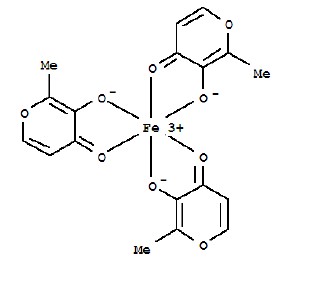 DRUG LABEL: ACCRUFER
NDC: 73059-001 | Form: CAPSULE
Manufacturer: Shield TX (UK) Ltd
Category: prescription | Type: HUMAN PRESCRIPTION DRUG LABEL
Date: 20260102

ACTIVE INGREDIENTS: FERRIC MALTOL 30 mg/1 1
INACTIVE INGREDIENTS: LACTOSE MONOHYDRATE; SODIUM LAURYL SULFATE; MAGNESIUM STEARATE; SILICON DIOXIDE; CROSPOVIDONE; HYPROMELLOSES; FD&C BLUE NO. 1; TITANIUM DIOXIDE; FD&C RED NO. 40; FD&C YELLOW NO. 6

HIGHLIGHTS OF PRESCRIBING INFORMATION

These highlights do not include all the information needed to use ACCRUFER® safely and effectively. See full prescribing information for ACCRUFER.
ACCRUFER (ferric maltol) capsules, for oral use
Initial U.S. Approval: 2019

1 INDICATIONS AND USAGE

ACCRUFER is an iron replacement product indicated for the treatment of iron deficiency in adult and pediatric patients 10 years of age and older. (1)

2 DOSAGE AND ADMINISTRATION

30 mg orally twice daily on an empty stomach 1 hour before or 2 hours after meals (2.1)

- Swallow capsules whole. Do not open, break, or chew capsules. (2.1)
- Continue as long as necessary to replenish body iron stores (2.1)

3 DOSAGE FORMS AND STRENGTHS

Capsules: 30 mg (3)

4 CONTRAINDICATIONS

- Hypersensitivity to the active substance or any excipient (4)
- Hemochromatosis and other iron overload syndromes (4)
- Patients receiving repeated blood transfusions (4)

5 WARNINGS AND PRECAUTIONS

- IBD Flare: Avoid use in patients with IBD flare (5.1)
- Iron Overload: Do not administer to patients with iron overload or those receiving intravenous iron. (5.2)
- Risk of Overdosage in Children Due to Accidental Ingestion: Keep out of reach of children. (5.3)

6 ADVERSE REACTIONS

Most common adverse reactions (incidence > 1%) are flatulence, diarrhea, constipation, feces discolored, abdominal pain, nausea, vomiting and abdominal discomfort/distension. (6.1)

To report SUSPECTED ADVERSE REACTIONS, contact Shield Therapeutics Inc at 1-888-963-6267 or FDA at 1-800-FDA-1088 or www.fda.gov/medwatch.

7 DRUG INTERACTIONS

- Dimercaprol: Avoid concomitant use. (7.2)
- Oral Medications: Separate administration of ACCRUFER from certain oral medications. Monitor clinical responses as appropriate. (7.1, 7.2)

RECENT MAJOR CHANGES

Indications and Usage (1) 12/2025

FULL PRESCRIBING INFORMATION

1 INDICATIONS AND USAGE

ACCRUFER is indicated for the treatment of iron deficiency in adult and pediatric patients 10 years of age and older.

2 DOSAGE AND ADMINISTRATION

2.1 Recommended Dosage

Adults and Children Aged 10 Years and Above

The recommended dosage of ACCRUFER is 30 mg orally twice daily, on an empty stomach 1 hour before or 2 hours after meals.

Swallow capsules whole. Do not open, break, or chew capsules.

Treatment duration will depend on the severity of iron deficiency but generally at least 12 weeks of treatment is required. The treatment should be continued as long as necessary until ferritin levels are within the normal range.

3 DOSAGE FORMS AND STRENGTHS

Capsules: ACCRUFER contains 30 mg iron, as ferric maltol, in red capsules printed with “30”.

4 CONTRAINDICATIONS

ACCRUFER is contraindicated in patients with a history of:

- Hypersensitivity to the active substance or to any of the excipients [see Description (11)] . Reactions could include shock, clinically significant hypotension, loss of consciousness, and/or collapse.
- Hemochromatosis and other iron overload syndromes [see Warnings and Precautions (5.1)] . Use may result in iron overdose [see Overdosage (10)].
- Receiving repeated blood transfusions. Use may result in iron overload [see Warnings and Precautions (5.2) and Overdosage (10)].

5 WARNINGS AND PRECAUTIONS

5.1 Increased Risk of Inflammatory Bowel Disease (IBD) Flare

Avoid use of ACCRUFER in patients with an active inflammatory bowel disease (IBD) flare, as there is potential risk of increased inflammation in the gastrointestinal tract.

5.2 Iron Overload

Excessive therapy with iron products can lead to excess storage of iron with the possibility of iatrogenic hemosiderosis. Do not administer ACCRUFER to patients with evidence of iron overload or patients receiving intravenous iron [see Contraindications (4)] . Assess iron parameters prior to initiating ACCRUFER and monitor iron parameters while on therapy [see Overdosage (10) and Clinical Pharmacology (12.2)] .

5.3 Risk of Overdosage in Children Due to Accidental Ingestion

Accidental overdose of iron-containing products is a leading cause of fatal poisoning in children under 6. Keep this product out of reach of children. In case of accidental overdose, call a doctor or poison control center immediately.

6 ADVERSE REACTIONS

The following clinically significant adverse reactions are described elsewhere in the labeling:

- Increased Risk of Inflammatory Bowel Disease Flare [see Warnings and Precautions (5.1)]
- Iron Overload [see Warnings and Precautions (5.2)]

6.1 Clinical Trials Experience

Because clinical trials are conducted under widely varying conditions, adverse reaction rates observed in the clinical trials of a drug cannot be directly compared to rates in the clinical trials of another drug and may not reflect the rates observed in practice.

The data described below reflect exposure to ACCRUFER in 175 adult patients in the placebo-controlled phase of three randomized studies conducted in patients with anemia and quiescent inflammatory bowel disease (IBD) (Studies AEGIS 1 & 2) or non-dialysis dependent chronic kidney disease (CKD) (AEGIS 3). The pooled patient population had a mean age of 58 years, 67.4% were female (n=118), and 81.7% (n=143) were Caucasian.

Table 1 presents all adverse reactions occurring in the placebo-controlled period of the pooled randomized studies [see Clinical Studies (14)] occurring at a rate of > 1% in the treated group, and for which the rate for ACCRUFER exceeds the rate for placebo.

Table 1. Adverse Reactions Reported by ≥1% of Patients Treated with ACCRUFER During Placebo-Controlled Period of Pooled Studies (Studies AEGIS1/2 and AEGIS 3)
 |  | ACCRUFER 30 mg Twice Daily (N = 175) | Placebo (N = 120)
Body System
 | Adverse Reaction
Gastrointestinal
 | Flatulence | 4.6% | 0.0%
 | Diarrhea | 4.0% | 1.7%
 | Constipation | 4.0% | 0.8%
 | Feces discolored | 4.0% | 0.8%
 | Abdominal pain | 2.9% | 2.5%
 | Nausea | 1.7% | 0.8%
 | Vomiting | 1.7% | 0.0%
 | Abdominal discomfort | 1.1% | 0.0%
 | Abdominal distension | 1.1% | 0.0%

The proportion of patients who discontinued treatment due to adverse reactions during the double-blind, placebo-controlled portion of studies was 4.6% for patients taking ACCRUFER. The most common adverse reaction leading to discontinuation of ACCRUFER in these studies was abdominal pain (1.7% of patients).

Pediatric Patients with Iron Deficiency Anemia

The safety profile of ACCRUFER in pediatric patients was assessed in 24 patients aged 10 to <18 years of age enrolled to the FORTIS trial and treated with ACCRUFER.

Overall, the safety profile reported in pediatric patients was consistent with the safety profile reported in adult patients with iron deficiency anemia.

7 DRUG INTERACTIONS

7.1 Effect of Other Drugs on ACCRUFER

Oral Medications

There are no empirical data on avoiding drug interactions between ACCRUFER and concomitant oral medications. Concomitant use of some drugs may reduce the bioavailability of iron after administration of ACCRUFER. Separate the administration of ACCRUFER from these drugs. The duration of separation may depend on the absorption characteristics of the medication concomitantly administered, such as time to peak concentration or whether the drug is an immediate or extended release product. Monitor clinical response to ACCRUFER.

7.2 Effect of ACCRUFER on Other Drugs

Dimercaprol

Concomitant use of iron products with dimercaprol may increase the risk of nephrotoxicity. Avoid concomitant use of ACCRUFER with dimercaprol.

Oral Medications

Concomitant use of ACCRUFER may decrease the bioavailability of some drugs, including mycophenolate, ethinyl estradiol, ciprofloxacin and doxycycline [see Clinical Pharmacology (12.3)] . For oral drugs where reductions in bioavailability may cause clinically significant effects on its safety or efficacy, separate the administration of ACCRUFER by at least 4 hours. Monitor clinical responses to concomitant drugs as appropriate.

8 USE IN SPECIFIC POPULATIONS

8.1 Pregnancy

Risk Summary

ACCRUFER is not absorbed systemically as an intact complex following oral administration, and maternal use is not expected to result in fetal exposure to the drug [see Clinical Pharmacology (12.3)] .

In animal reproduction studies, oral administration of ferric or ferrous compounds to gravid CD1-mice and Wistar-rats during organogenesis at doses 13 to 32 times the recommended human dose resulted in no adverse developmental outcomes. An overdose of iron in pregnant women may carry a risk for spontaneous abortion, gestational diabetes and fetal malformation (see Data).

In animal reproduction studies, oral administration of maltol to pregnant Crl: COBS-CD (SD) BR rats during organogenesis at doses 6 times the recommended human dose resulted in no adverse developmental outcomes (see Data).

The estimated background risk of major birth defects and miscarriage for the indicated population is unknown. All pregnancies have a background risk of birth defect, loss, or other adverse outcomes. In the U.S. general population, the estimated background risk of major birth defects and miscarriage in clinically recognized pregnancies is 2-4% and 15-20%, respectively.

Clinical Considerations

Disease-Associated Maternal and/or Embryo/Fetal Risk

Untreated iron deficiency anemia (IDA) in pregnancy is associated with adverse maternal outcomes such as post-partum anemia. Adverse pregnancy outcomes associated with IDA include increased risk for preterm delivery and low birth weight.

Data

Animal Data

In embryofetal development studies in mice and rats, pregnant animals received oral doses of ferric or ferrous compounds (ferrous sulfate or ferric sodium pyrophosphate) of up to 160 mg/kg/day in mice, or up to 200 mg/kg/day in rats, during the period of organogenesis. Administration of ferric or ferrous compounds at doses 13 times (in mice) or 32 times (in rats) the recommended human dose resulted in no maternal toxicity and no adverse developmental outcomes.

In a multigeneration reproductive and developmental study in rats, pregnant animals received oral doses of maltol of 100, 200, and 400 mg/kg/day, during the period of organogenesis. Administration of maltol at doses 6 times the recommended human dose resulted in no maternal toxicity and no adverse developmental outcomes.

8.2 Lactation

Risk Summary
There are no data on the presence of ACCRUFER in human milk, the effects on the breastfed child, or the effects on milk production. ACCRUFER is not absorbed systemically as an intact complex by the mother following oral administration, and breastfeeding is not expected to result in exposure of the child to ACCRUFER.

8.4 Pediatric Use

The safety and effectiveness of ACCRUFER for the treatment of iron deficiency have been established in pediatric patients 10 years and older. Use of ACCRUFER for this indication is supported by evidence from adequate and well-controlled studies of ACCRUFER in adults with additional data from an adequate and well-controlled study conducted in pediatric patients aged 10 years and older [see Clinical Studies (14.3)].

Safety and effectiveness of ACCRUFER have not been established in pediatric patients under 10 years.

8.5 Geriatric Use

Of the 295 patients in the randomized trials of ACCRUFER, 39% of patients were aged 65 and older, while 23% were aged 75 and older. No overall differences in safety or effectiveness were observed between these patients and younger patients.

10 OVERDOSAGE

No data are available regarding overdose of ACCRUFER in patients. Acute iron ingestion of 20 mg/kg elemental iron is potentially toxic and 200- 250 mg/kg is potentially fatal. Early signs and symptoms of iron overdose may include nausea, vomiting, abdominal pain and diarrhea. In more serious cases there may be evidence of hypoperfusion, metabolic acidosis and systemic toxicity.

Dosages of ACCRUFER in excess of iron needs may lead to accumulation of iron in storage sites leading to hemosiderosis. Periodic monitoring of iron parameters such as serum ferritin and transferrin saturation may assist in recognizing iron accumulation. Do not administer ACCRUFER to patients with iron overload [see Contraindications (4) ].

Consider contacting the Poison Help line (1-800-222-1222) or a medical toxicologist for additional overdose management recommendations.

11 DESCRIPTION

ACCRUFER (ferric maltol) capsules, an iron replacement product for oral administration, contain 30 mg iron and 201.5 mg maltol. Ferric maltol contains iron in a stable ferric state as a complex with a trimaltol ligand. Ferric maltol is 3-hydroxy-2-methyl-4H-pyrane-4-one iron (III) complex (3:1) and has the molecular formula (C6H5O3)3Fe and a molecular mass of 431.2.

Each red capsule, printed with “30”, contains colloidal anhydrous silica, crospovidone (Type A), lactose monohydrate, magnesium stearate and sodium lauryl sulfate as inactive ingredients. In addition, the capsule shell contains FD&C Blue No. 1, FD&C Red No. 40, FD&C Yellow No.6, hypromellose and titanium dioxide. The ink used for printing the marking contains Shellac, ammonium hydroxide, ethanol, iron oxide black and propylene glycol.

12 CLINICAL PHARMACOLOGY

12.1 Mechanism of Action

ACCRUFER delivers iron for uptake across the intestinal wall and transfer to transferrin and ferritin.

12.2 Pharmacodynamics

ACCRUFER has been shown to increase serum iron parameters, including ferritin and transferrin saturation (TSAT) in adults and pediatric patients 10 years and older.

12.3 Pharmacokinetics

Adults

The pharmacokinetic properties of serum iron after administration of ACCRUFER was assessed in subjects with iron deficiency (with or without anemia) following a single dose and at steady state (after 1 week) of ACCRUFER 30 mg, 60 mg, or 90 mg twice daily (1 to 3 times the approved recommended dosage). Total serum iron concentrations increase in a less than dose proportional manner with increasing ACCRUFER doses. Total serum iron peak values were reached 1.5 to 3 hours after administration of ACCRUFER, and were comparable between Day 1 and Day 8.

Pediatric Population

In a pharmacokinetic substudy of the FORTIS trial [see Clinical Studies (14.3)] in pediatric patients with iron-deficiency anemia, ferric maltol 15 mg or 30 mg was administered orally twice daily, for 7-10 days in children aged 10 to <18 years. After a single dose of 30 mg on Day 1, baseline-corrected serum iron reached peak concentration (Cmax = 119 µg/dL) at 2 hours, with a AUC0-t of 374 h·µg/dL in children aged 12 to <18 years. After a single dose of 15 mg on Day 1, baseline-corrected serum iron reached peak concentration (Cmax = 40 µg/dL) at 2.1 hours, with a AUC0-t of 60.1 h·µg/dL in children aged 10 to 11 years. No accumulation of maltol glucuronide was observed.

Absorption

ACCRUFER dissociates upon uptake from the gastrointestinal tract allowing iron and maltol to be absorbed separately.

Effect of Food

Food has been shown to decrease the bioavailability of iron after administration of ferric maltol capsules.

Drug Interaction Studies

In vitro

Of the drugs screened for an interaction with ferric maltol in vitro at pH 1.2, 4.5 and 6.8, only mycophenolate and ethinyl estradiol showed any potential for interaction. Mycophenolate recovery was reduced by up to 16% at pH 1.2 but there was no interaction at pH 4.5; due to solubility issues data are not available for pH 6.8. Ethinyl estradiol recovery was reduced by up to 35% at pH 4.5; due to solubility issues data are not available for pH 1.2 and pH 6.8. These potential oral interactions can be avoided by spacing the administration of those drugs and ACCRUFER [see Drug Interactions (7.2)] .

Lisinopril, metoprolol and warfarin showed no interaction at any of the 3 pH conditions and can be taken with ACCRUFER.

No interaction with ferric maltol was observed for atorvastatin (pH 6.8), and norgestimate (pH 1.2) (data were not obtainable at the other pH conditions due to solubility issues).

In vivo

No clinical studies evaluating the drug interaction potential of ACCRUFER have been conducted.

Iron-containing preparations may decrease ciprofloxacin absorption into the bloodstream, resulting in lower serum and urine levels and reduced effectiveness.

Absorption of tetracyclines including doxycycline is reported to be impaired by iron-containing preparations.

12.6 Maltol Phamacokinetics

Maltol is metabolized through glucuronidation (UGT1A6) and sulphation in vitro. Of the total maltol ingested, a mean of between 39.8% and 60% was excreted in the urine as maltol glucuronide. There was no clinically meaningful change in exposure of maltol or maltol glucuronide in subjects with non-dialysis dependent chronic kidney disease (eGFR of >15 mL/min/1.73m^2and <60 mL/min/1.73m^2).

13 NONCLINICAL TOXICOLOGY

13.1 Carcinogenesis, Mutagenesis, Impairment of Fertility

Ferric Maltol

ACCRUFER is not absorbed systemically as an intact complex.

Carcinogenicity studies have not been conducted with ferric maltol.

Ferric maltol was mutagenic in vitro in reverse bacterial mutation (Ames) assays. Ferric maltol increased revertant frequency in the absence and presence of metabolic activation.

Fertility studies have not been conducted with ferric maltol.

Maltol

The carcinogenic potential of maltol has been evaluated in long-term animal toxicity studies in two species: CD-1 mice and Sprague-Dawley rats. Maltol was not carcinogenic in a 18-month study in mice at doses up to 400 mg/kg (approximately 5.6 times the human daily dose). Maltol was not carcinogenic in a 2-year study in rats at doses up to 400 mg/kg (approximately 11.2 times the human daily dose).

Maltol was mutagenic in vitro in reverse bacterial mutation (Ames) assays. Maltol increased revertant frequency in the absence and presence of metabolic activation. Maltol was clastogenic in vivo in a mouse micronucleus assay (increase in polychromatic erythrocytes) at intraperitoneal doses of 774 mg/kg. Absorbed maltol is rapidly conjugated with glucuronic acid. It is therefore unlikely that the mutagenic activity of maltol would be expressed under the conditions of oral human intake.

In a multi-generation animal reproduction study in male and female rats, there were no effects on mating, fertility, or early embryonic development at doses up to 400 mg/kg/day (approximately 11.2 times the human daily dose).

14 CLINICAL STUDIES

14.1 Patients with Inflammatory Bowel Disease (IBD)

The safety and efficacy of ACCRUFER for the treatment of iron deficiency anemia was studied in two randomized, placebo-controlled trials: AEGIS 1 (NCT01252221) and AEGIS 2 (NCT01340872). These trials enrolled 128 patients (age range 18-76 years; 45 males and 83 females) with quiescent IBD (58 patients with Ulcerative Colitis [UC] and 70 patients with Crohns disease [CD]) and baseline Hb concentrations between 9.5 g/dL and 12 /13 g/dL for females / males and ferritin < 30 mcg/L. All patients had discontinued prior oral ferrous product treatment due to lack of efficacy or inability to tolerate oral iron replacement products. Subjects were randomized 1:1 to receive either 30 mg ACCRUFER twice daily or a matched placebo control for 12 weeks.) and AEGIS 2 (NCT01340872). These trials enrolled 128 patients (age range 18-76 years; 45 males and 83 females) with quiescent IBD (58 patients with Ulcerative Colitis [UC] and 70 patients with Crohns disease [CD]) and baseline Hb concentrations between 9.5 g/dL and 12 /13 g/dL for females / males and ferritin < 30 mcg/L. All patients had discontinued prior oral ferrous product treatment due to lack of efficacy or inability to tolerate oral iron replacement products. Subjects were randomized 1:1 to receive either 30 mg ACCRUFER twice daily or a matched placebo control for 12 weeks.

The major efficacy outcome was the mean difference in Hb concentration from baseline to week 12 between ACCRUFER and placebo. The Least Square [LS] mean difference from baseline was 2.18 g/dL (p<0.0001)(see Table 2).

Table 2. Summary of Hemoglobin Concentration (g/dL) and Change from Baseline to Week 12 AEGIS 1 & 2 - Analysis Using Multiple Imputation - Full Analysis Set Population
Visit (Week); Statistic | ACCRUFER (N = 64) | Placebo (N =64)
Baseline
Mean (SD) | 11.0 (1.03) | 11.10 (0.85)
Mean change from baseline to Week 12
LS Mean (SE) | 2.25 (0.12) | 0.06 (0.13)
Treatment Comparison | Difference in Change from Baseline
Treatment Comparison | LSM Difference (SE) ACCRUFER Placebo) | 1-sided lower 97.5%CI | p-value
ACCRUFER versus placebo | 2.18 (0.19) | (1.81) | <0.0001
Note: Multiple imputation was based on treatment, gender, disease [UC or CD], and Hb concentration at baseline, Week 4, and 8. For each imputed dataset, the change from baseline to Week 12 was analyzed using an ANCOVA model with treatment as the factor and gender, disease, baseline Hb concentration as covariates.

The LS mean difference in change from baseline Hb to Week 4 and 8 between ACCRUFER and placebo were 1.04 g/dl and 1.73 g/dl, respectively.

The mean ferritin (mcg/L) levels in ACCRUFER subjects at baseline were 8.6 mcg/L [SD 6.77]) and the mean ferritin (mcg/L) levels at Week 12 were 26.0 mcg/L [SD 30.57] with a mean overall improvement of 17.3 mcg/L.

Following completion of the 12-week placebo-controlled phase of the studies, eligible patients transitioned to ACCRUFER 30 mg twice daily open-label treatment for an additional 52 weeks.

During the open-label phase with ACCRUFER, the mean change in Hb concentration from baseline to Week 64 was 3.1 g/dL [SD 1.46 g/dL, n = 35] and the ferritin value demonstrated a mean of 68.9 mcg/L [SD 96.24] at 64 weeks, with a mean overall improvement of 60.4 mcg/L.

14.2 Patients with Chronic Kidney Disease (CKD)

The safety and efficacy of ACCRUFER for the treatment of iron deficiency anemia was studied in AEGIS 3 (NCT02968368), a trial that enrolled 167 patients (mean age 67.4 years, range 30-90 years; 50 males and 117 females) with non-dialysis dependent chronic kidney disease (CKD) and baseline hemoglobin (Hb) concentrations between 8g/dL and 11 g/dL and ferritin < 250 mcg/L with a Transferrin saturation (TSAT) <25% or ferritin < 500 mcg/L with a TSAT <15%. ACCRUFER was administered at a dose of 30 mg twice daily. Subjects were randomized 2:1 to receive either 30 mg ACCRUFER twice daily or a matched placebo control for 16 weeks.

The major efficacy outcome was the mean difference in Hb concentration from baseline to Week 16 between ACCRUFER and placebo. The LS mean difference was 0.52 g/dL (p= 0.0149) (see Table 3).

Table 3. Summary of Hemoglobin Concentration (g/dL) and Change from Baseline to Week 16 Analysis Using Multiple Imputation Intent-to-Treat Population
Visit (Week); Statistic | ACCRUFER (N = 111) | Placebo (N = 56)
Baseline
Mean (SD) | 10.06 (0.77) | 10.03 (0.82)
Mean change from baseline to Week 16
LS Mean (SE) | 0.50 (0.12) | -0.02 (0.16)
Treatment Comparison | Difference in Change from Baseline
Treatment Comparison | LSM Difference (SE) ACCRUFER – Placebo | 95% CI | p-value
ACCRUFER versus placebo | 0.52 (0.21) | (0.10, 0.93) | 0.0149
Note: Multiple imputation was based on treatment, gender, eGFR at baseline, and Hb concentration at baseline, Week 4 and 8. For each imputed dataset, the change from baseline to Week 16 was analyzed using an ANCOVA model with treatment as the factor and baseline Hb concentration, baseline eGFR as covariates.

The LS mean difference in change from baseline Hb to Week 4 and 8 between ACCRUFER and placebo were 0.13 g/dl and 0.46 g/dl, respectively.

The mean change in ferritin concentration from baseline to Week 16 was 49.3 mcg/L for the ACCRUFER group and 6.3 mcg/L for the placebo group. The mean difference for ACCRUFER versus placebo was 43.0 mcg/L.

14.3 Pediatric Patients with Iron Deficiency Anemia

The efficacy of ACCRUFER for the treatment of iron deficiency was evaluated in 24 patients aged 10 to <18 (age range 10-17 years; 4 males and 20 females; 13 White, 8 Black or African American, 2 Asian, 1 Other; 10 Hispanic or Latino, 14 Not Hispanic or Latino) with iron deficiency anemia who received aged-based dosing of ACCRUFER twice daily in the FORTIS study. Patients aged 10-11 years received 15 mg twice daily while patients 12 to <18 years received 30 mg twice daily.

Efficacy was assessed based on mean change from baseline to week 12 in Hb (g/dL) (descriptive statistics). A clinically significant increase in Hb was observed in children 10 years and above receiving ACCRUFER orally twice daily for 12 weeks (see Table 4). The results are presented for the pooled population who received either 15 mg twice daily or 30 mg orally twice daily (based on age). The 15 mg twice daily dose is not approved and not recommended for use. The recommended dosage of ACCRUFER in pediatric patients aged 10 years and over is 30 mg orally twice daily.

Table 4. Summary of Hemoglobin Concentration (g/dL) and Change from Baseline to Week 12 in Pediatric Patients with Iron Deficiency Anemia in the FORTIS Studya
Endpoint | ACCRUFER 10 to <18 years (N=24)
Hb concentrations (g/dL)
Baseline (SD) | 10.73 (0.89)
Mean change from baseline to week 12b | 1.10 (1.06)

a Subset of patients in the 10 to <18 subgroup
b Modified-Intent to Treat (mITT) population: all subjects who received at least 1 dose of study drug
The mean change in Hb at week 12 in the subgroup (N=21) who received the recommended dose of ACCRUFER 30 mg orally twice daily was 1.23 g/dL [SD 1.00].
The mean ferritin levels in ACCRUFER subjects aged 10 to <18 years (N=24) at baseline were 11.4 mcg/L [SD 10.06] and the mean ferritin levels at Week 12 were 20 mcg/L [SD 13.51] with a mean overall improvement of 8.6 mcg/L [SD 10.29].

16 HOW SUPPLIED/STORAGE AND HANDLING

16.1 How Supplied

ACCRUFER (ferric maltol) 30 mg iron capsules are supplied as 60 red capsules, printed with “30”, in HDPE bottles with a child-proof polypropylene push-lock.

1 Bottle of 60-count 30 mg ferric iron capsules (NDC 73059-001-60).

16.2 Storage and Handling

Store at 20°C to 25°C (68°F to 77°F); excursions permitted to 15°C to 30°C (59°F to 86°F) [See USP controlled room temperature].

17 PATIENT COUNSELING INFORMATION

Advise the patient to read the FDA-approved patient labeling (Patient Information).

Administration

- Inform patients to take ACCRUFER as directed on an empty stomach 1 hour before or 2 hours after meals. Instruct patients on concomitant medications that should be dosed apart from ACCRUFER [see Dosage and Administration (2.1) and Drug Interactions (7.2)] .
- Advise patients to swallow the capsules whole and not to open, break, or chew capsules.

Adverse Reactions

Advise patients that ACCRUFER may cause, flatulence, diarrhea, constipation, discolored feces, abdominal pain, nausea, vomiting or abdominal bloating or discomfort. Advise patients to report severe or persistent gastrointestinal symptoms or any allergic reactions to their physician [see Adverse Reactions (6.1)].

Increased Risk of IBD Flare

Advise patients that they should not use ACCRUFER if they are experiencing an IBD flare [see Warnings and Precautions (5.1)] .

Iron Overload and Risk of Accidental Overdose in Children

Inform patients to keep this product out of reach of children as accidental overdose of iron products is a leading cause of fatal poisonings in children. In case of accidental overdose, advise them to call a doctor or poison control center immediately [see Warnings and Precautions (5.2,5.3)].

Distributed by Shield Therapeutics Inc, 7-57 Wells Avenue Newton, MA, 02459

Patient Information

ACCRUFER®(ak-roo-fer)
(ferric maltol)
capsules

What is ACCRUFER?

ACCRUFER is a prescription medicine used in adults and children 10 years of age and older to treat low iron stores in your body.

It is not known if ACCRUFER is safe and effective in children under 10 years of age.

Do not take ACCRUFER if you:

- are allergic to ferric maltol or any of the ingredients in ACCRUFER. See the end of this leaflet for a complete list of ingredients in ACCRUFER.
- have any illness that causes you to store too much iron in your body or if you have a problem with how your body uses iron.
- are receiving repeated blood transfusions.

Before taking ACCRUFER, tell your healthcare provider about all your medical conditions, including if you:

- have inflammatory bowel disease (IBD).
- are pregnant or plan to become pregnant. It is not known if ACCRUFER will harm your unborn baby.
- are breastfeeding or plan to breastfeed. It is not known if ACCRUFER passes into your breast milk and may harm your baby. Talk to your healthcare provider about the best way to feed your baby during treatment with ACCRUFER.

Tell your healthcare provider about all the medicines you take, including prescription and over-the-counter medicines, vitamins, and herbal supplements.

Taking ACCRUFER with certain other medicines may affect each other causing serious side effects.

You may need to take ACCRUFER at least 4 hours before or 4 hours after you take certain medicines. Ask your healthcare provider for a list of these medicines if you are not sure if you take one of these medicines.

Especially tell your healthcare provider if you take:

- dimercaprol
- other oral iron tablets or health supplements containing iron

Ask your healthcare provider if you are not sure if you take one of these medicines.

Know the medicines you take. Keep a list of them to show to your healthcare provider and pharmacist when you get a new medicine.

How should I take ACCRUFER?

- Take ACCRUFER exactly as your healthcare provider tells you to.
- Take ACCRUFER 2 times a day on an empty stomach 1 hour before or 2 hours after meals.
- Swallow ACCRUFER capsules whole. Do not open, break, or chew ACCRUFER capsules.
- In case of accidental overdose, call your healthcare provider or Poison Help line at 1-800-222-1222 or go to the nearest hospital emergency room right away.

What are the possible side effects of ACCRUFER?

ACCRUFER may cause serious side effects, including:

- Increased risk of inflammatory bowel disease (IBD) flare.You should avoid taking ACCRUFER if you have inflammatory bowel disease (IBD) and are experiencing a flare.
- Too much iron stored in your body (iron overload).Your healthcare provider should check the iron level in your blood before you start and during treatment with ACCRUFER.
- Risk of overdose in children due to accidental swallowing.Accidental overdose of iron-containing products is a leading cause of death from poisoning in children under 6. Keep ACCRUFER in a safe place and out of the reach of children.

The most common side effects of ACCRUFER include:

- gas

- diarrhea

- constipation

- discolored stools

- stomach pain

- nausea

- vomiting

- stomach area discomfort or bloating

These are not all the possible side effects of ACCRUFER.

Call your doctor for medical advice about side effects. You may report side effects to FDA at 1-800-FDA-1088.

How should I store ACCRUFER?

- Store ACCRUFER at room temperature between 68°F to 77°F (20°C to 25°C).
- ACCRUFER comes in a child-resistant bottle.

Keep ACCRUFER and all medicines out of reach of children.

General information about the safe and effective use of ACCRUFER.

Medicines are sometimes prescribed for purposes other than those listed in a Patient Information leaflet. Do not use ACCRUFER for a condition for which it was not prescribed. Do not give ACCRUFER to other people, even if they have the same symptoms that you have. It may harm them. You can ask your healthcare provider or pharmacist for information about ACCRUFER that is written for health professionals.

What are the ingredients in ACCRUFER?

Active ingredient: ferric maltol

Inactive ingredients:

Capsule: colloidal anhydrous silica, crospovidone (Type A), lactose monohydrate, magnesium stearate, sodium lauryl sulfate

Capsule Shell: FD&C Blue No. 1 FD&C Red No. 40, FD&C Yellow 6, hypromellose, titanium dioxide.

Ink: Shellac, ammonium hydroxide, ethanol, iron oxide black, propylene glycol

Distributed by Shield Therapeutics Inc, 7-57 Wells Avenue Newton, MA, 02459

US Patents 7459569, 9248148, 9802973, 10179120

This Patient Information has been approved by the U.S. Food and Drug Administration.
Revised: December 2025

PRINCIPAL DISPLAY PANEL - 60 Capsules

Carton Label - ACCRUFER®(ferric maltol) capsules 30 mg (60 Capsules)

NDC 73059-001-60

ACCRUFeR®
(ferric maltol*)
capsules
30 mg

For oral
administration only

60 capsules

Distributed by
Shield Therapeutics Inc

SHIELD
THERAPEUTICS

Rx only

Bottle Label - ACCRUFER®(ferric maltol) capsules 30 mg

NDC73059-001-60
ACCRUFeR®
(ferric maltol*)
capsules
30 mg
For oral administration only

60 capsules

SHIELD
THERAPEUTICS

Rx only

*Each capsule contains 30 mg iron (as
ferric maltol)

WARNING:Accidental overdose of
iron-containing products is a leading
cause of fatal poisoning in children
under 6. Keep this product out of reach
of children. In case of accidental
overdose, call a doctor or poison control
center immediately.

Store at 20°C to 25°C (68°F to 77°F);

excursions permitted to 15°C to 30°C
(59°F to 86°F). (See USP controlled room
temperature).
Usual Dosage: 1 capsule twice daily on an
empty stomach. See prescribing information.
Distributed by Shield Therapeutics Inc.

PRINCIPAL DISPLAY PANEL - 10 Capsules

Carton Label - ACCRUFER ® (ferric maltol) capsules 30 mg (10 Capsules)

NDC 73059-001-10

ACCRUFeR®
(ferric maltol*)

capsules

30 mg

For oral
administration only

10 capsules

Professional Sample -
Not For Sale

SHIELD
THERAPEUTICS

Rx only

Bottle Label - ACCRUFER ® (ferric maltol) capsules 30 mg (10 Capsules)

NDC 73059-001-10
ACCRUFeR®
(ferric maltol*) 30 mg capsules
For oral administration
only

10 capsules

Sample-Not for Sale

SHIELD
THERAPEUTICS

Rx only

*Each capsule contains 30 mg iron (as ferric maltol).

Store at 20°C to 25°C (68°F to 77°F);

Usual Dosage: 1 capsule twice daily on an
empty stomach. See Prescribing Information.

Distributed by Shield Therapeutics Inc.